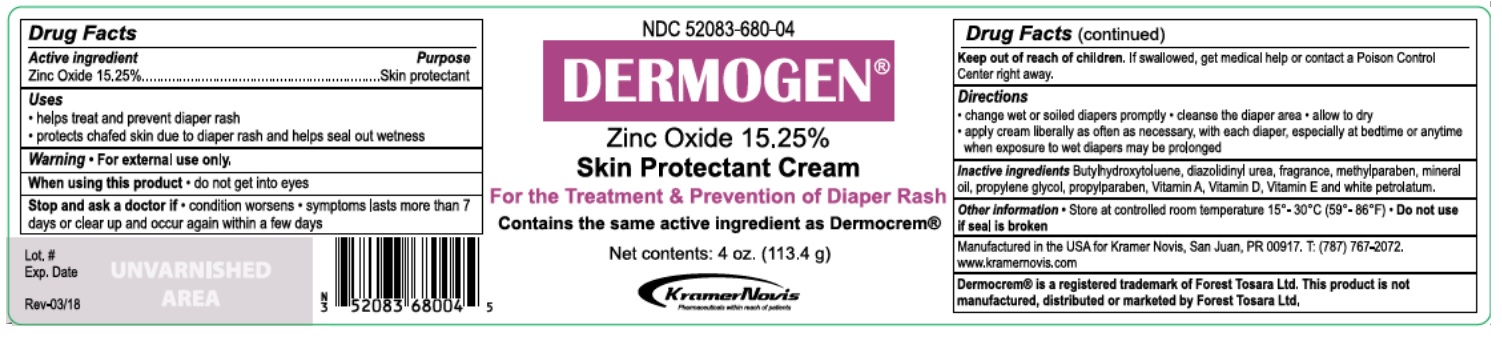 DRUG LABEL: DERMOGEN
NDC: 52083-680 | Form: CREAM
Manufacturer: KRAMER NOVIS
Category: otc | Type: HUMAN OTC DRUG LABEL
Date: 20251114

ACTIVE INGREDIENTS: ZINC OXIDE 15.25 g/100 g
INACTIVE INGREDIENTS: BUTYLATED HYDROXYTOLUENE; DIAZOLIDINYL UREA; METHYLPARABEN; MINERAL OIL; PROPYLENE GLYCOL; PROPYLPARABEN; VITAMIN A; VITAMIN D; .ALPHA.-TOCOPHEROL; PETROLATUM

DERMOGEN (Zinc Oxide Cream)

Active ingredient

Zinc Oxide 15.25%

Purpose

Skin protectant

Uses

• helps treat and prevent diaper rash

• protects chafed skin due to diaper rash and helps seal out wetness

Warning

• For external use only.

When using this product • do not get into eyes

Stop and ask a doctor if • condition worsens • symptoms lasts more than 7 days or clear up and occur again within a few days

Keep out of reach of children. If swallowed, get medical help or contact a Poison Control Center right away.

Directions

• change wet or soiled diapers promptly. • cleanse the diaper area • allow to dry • apply cream liberally as often as necessary, with each diaper, especially at bedtime or anytime when exposure to wet diapers may be prolonged

Inactive ingredients

Butylhydroxytoluene, diazolidinyl urea, fragrance, methylparaben, mineral oil, propylene glycol, propylparaben, Vitamin A, Vitamin D, Vitamin E and white petrolatum.

Other information

• Store at controlled room temperature 15°-30°C (59°-86°F) • Do not use if seal is broken

For the Treatment & Prevention of Diaper Rash

Contains the same active ingredient as Dermocrem®

Manufactured in the USA for Kramer Novis,
San Juan, PR 00917. T: (787) 767-2072.
www.kramernovis.com

Dermocrem® is a registered trademark of Forest Tosara Ltd. This product is not manufactured, distributed or marketed by Forest Tosara Ltd.